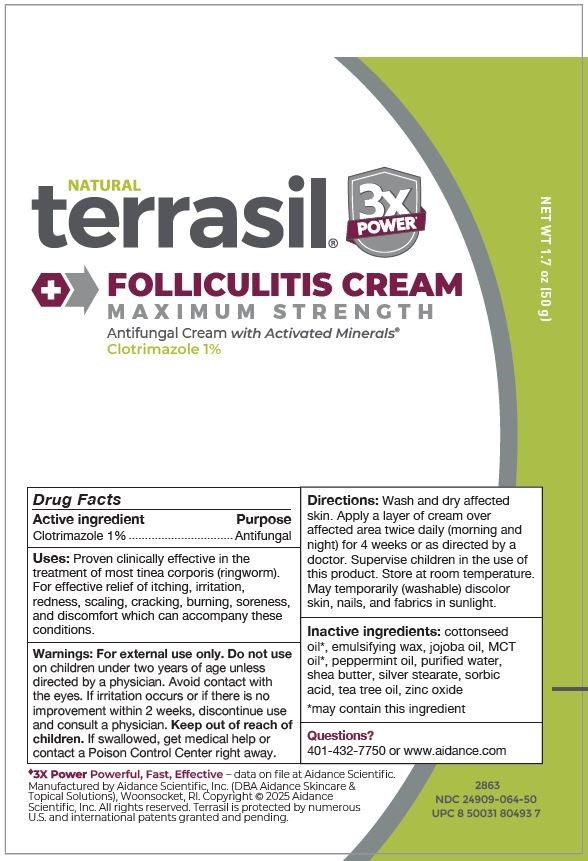 DRUG LABEL: terrasil Folliculitis Cream
NDC: 24909-064 | Form: CREAM
Manufacturer: Aidance Scientific, Inc., DBA Aidance Skincare & Topical Solutions
Category: otc | Type: HUMAN OTC DRUG LABEL
Date: 20250523

ACTIVE INGREDIENTS: CLOTRIMAZOLE 1 g/100 g
INACTIVE INGREDIENTS: JOJOBA OIL; SORBIC ACID; CETOSTEARYL ALCOHOL; PEPPERMINT OIL; COTTONSEED OIL; SILVER STEARATE; SHEA BUTTER; TEA TREE OIL; WATER; ZINC OXIDE

24909-064 terrasil Folliculitis Cream Max

Active Ingredient

Clotrimazole 1%

Purpose

Antifungal

Uses

Proven clinically effective in the treatment of most tinea corporis (ringworm). For effective relief of itching, irritation, redness, scaling, cracking, burning, soreness, and discomfort which can accompany these conditions.

Warnings

For external use only. Do not use on children under two years of age unless directed by a physician. Avoid contact with the eyes. If irritation occurs or if there is no improvement within 2 weeks, discontinue use and consult a physician.

Keep out of reach of children.

OTHER SAFETY INFORMATION

If swallowed, get medical help or contact a Poison Control Center right away.

Directions

Wash and dry affected skin. Apply a layer of cream over affected area twice daily (morning and night) for 4 weeks or as directed by a doctor. Supervise children in the use of this product. Store at room temperature. May temporarily (washable) discolor skin, nails, and fabrics in sunlight.

Inactive Ingredients

cottonseed oil*, emulsifying wax, jojoba oil, MCT oil*, peppermint oil, purified water, shea butter, silver stearate, sorbic acid, tea tree oil, zinc oxide

*may contain this ingredient

Questions?

401-432-7750 or www.aidance.com